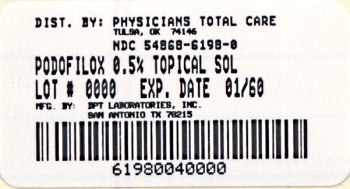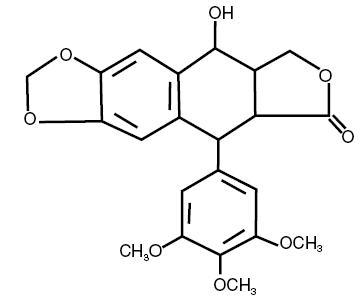 DRUG LABEL: Podofilox
NDC: 54868-6198 | Form: SOLUTION
Manufacturer: Physicians Total Care, Inc.
Category: prescription | Type: HUMAN PRESCRIPTION DRUG LABEL
Date: 20100121

ACTIVE INGREDIENTS: PODOFILOX 5 mg/1 mL
INACTIVE INGREDIENTS: LACTIC ACID; SODIUM LACTATE; ALCOHOL

Podofilox
0.5% Topical Solution
Rx only

DESCRIPTION

Podofilox is an antimitotic drug which can be chemically synthesized or purified from the plant families Coniferae and Berberidaceae (e.g. species of Juniperus and Podophyllum). Podofilox 0.5% Solution is formulated for topical administration. Each milliliter of solution contains 5 mg of podofilox, in a vehicle containing lactic acid and sodium lactate in alcohol 95%, USP.

Podofilox has a molecular weight of 414.4 daltons, and is soluble in alcohol and sparingly soluble in water. Its chemical name is 5,8,8a,9-Tetrahydro-9-hydroxy-5-(3,4,5-trimethoxyphenyl)furo[3',4':6,7] naphtho[2,3,d]-1, 3-dioxol-6(5aH)-one. Podofilox has the following structural formula:

CLINICAL PHARMACOLOGY

Mechanism of Action

Treatment of genital warts with podofilox results in necrosis of visible wart tissue. The exact mechanism of action is unknown.

Pharmacokinetics

In systemic absorption studies in 52 patients, topical application of 0.05 mL of 0.5% podofilox solution to external genitalia did not result in detectable serum levels. Applications of 0.1 to 1.5 mL resulted in peak serum levels of 1 to 17 ng/mL one to two hours after application. The elimination half-life ranged from 1 to 4.5 hours. The drug was not found to accumulate after multiple treatments.

CLINICAL STUDIES

In clinical studies with Podofilox 0.5% Solution, the test product and its vehicle were applied in a double-blind fashion to comparable patient groups. Patients were treated for two to four weeks, and reevaluated at a two-week follow-up examination. Although the number of patients and warts evaluated at each time period varied, the results among investigators were relatively consistent.

The following table represents the responses noted in terms of frequency of response by lesions treated and the overall response by patients. Data are presented for the 2-week follow-up only for those patients evaluated at that time point.

Responses in Treated Patients
 | Initially | Recurred after | Cleared
 | Cleared* | Clearing* | at 2-Week Follow-up*
% Warts | 79% | 35% | 60%
(n=524) | (412/524) | (146/412) | (269/449)
% Patients | 50% | 60% | 25%
(n=70) | (35/70) | (21/35) | (14/57)
*Cleared and clearing mean no visible wart tissue remained at the treated sites

INDICATIONS AND USAGE

Podofilox 0.5% Solution is indicated for the topical treatment of external genital warts (Condyloma acuminatum). This product is not indicated in the treatment of perianal or mucous membrane warts (see PRECAUTIONS).

Diagnosis

Although genital warts have a characteristic appearance, histopathologic confirmation should be obtained if there is any doubt of the diagnosis. Differentiating warts from squamous cell carcinoma (so-called “Bowenoid papulosis”) is of particular concern. Squamous cell carcinoma may also be associated with human papillomavirus but should not be treated with Podofilox 0.5% Solution.

CONTRAINDICATIONS

Podofilox 0.5% Solution is contraindicated for patients who develop hypersensitivity or intolerance to any component of the formulation.

WARNINGS

Correct diagnosis of the lesions to be treated is essential. See the “Diagnosis” subsection of the INDICATIONS AND USAGE statement.

Podofilox 0.5% Solution is intended for cutaneous use only. Avoid contact with the eye. If eye contact occurs, patients should immediately flush the eye with copious quantities of water and seek medical advice.

PRECAUTIONS

General

Data are not available on the safe and effective use of this product for treatment of warts occurring in the perianal area or on mucous membranes of the genital area (including the urethra, rectum and vagina). The recommended method of application, frequency of application, and duration of usage should not be exceeded (see DOSAGE AND ADMINISTRATION).

Information for Patients

The patient should be provided with a Patient Information leaflet when a podofilox prescription is filled.

Carcinogenesis, Mutagenesis, Impairment of Fertility

Reports of lifetime carcinogenicity studies in mice are not available. Published animal studies, in general, have not shown the drug substance, podofilox, to be carcinogenic.^1,2,3,4,5 There are published reports that, in mouse studies, crude podophyllin resin (containing podofilox) applied topically to the cervix produced changes resembling carcinoma in situ.^6 These changes were reversible at five weeks after cessation of treatment. In one reported experiment, epidermal carcinoma of the vagina and cervix was found in 1 out of 18 mice after 120 applications of podophyllin^7 (the drug was applied twice weekly over a 15-month period).

Podofilox was not mutagenic in the Ames plate reverse mutation assay at concentrations up to 5 mg/plate, with and without metabolic activation. No cell transformation related to potential oncogenicity was observed in BALB/3T3 cells after exposure to podofilox at concentrations up to 0.008 mcg/mL without metabolic activation and 12 mcg/mL podofilox with metabolic activation. Results from the mouse micronucleus in vivo assay using podofilox 0.5% solution in concentrations up to 25 mg/kg, indicate that podofilox should be considered a potential clastogen (a chemical that induces disruption and breakage of chromosomes).

Daily topical application of Podofilox 0.5% Solution at doses up to the equivalent of 0.2 mg/kg (5 times the recommended maximum human dose) to rats throughout gametogenesis, mating, gestation, parturition and lactation for two generations demonstrated no impairment of fertility.

Pregnancy

Pregnancy Category C: Podofilox was not teratogenic in the rabbit following topical application of up to 0.21 mg/kg (5 times the maximum human dose) once daily for 13 days. The scientific literature contains references that podofilox is embryotoxic in rats when administered systemically in a dose approximately 250 times the recommended maximum human dose.^8,9 Teratogenicity and embryotoxicity have not been studied with intravaginal application. Many antimitotic drug products are known to be embryotoxic. There are no adequate and well-controlled studies in pregnant women. Podofilox should be used in pregnancy only if the potential benefit justifies the potential risk to the fetus.

Nursing Mothers

It is not known whether this drug is excreted in human milk. Because of the potential for serious adverse reactions in nursing infants from podofilox, a decision should be made whether to discontinue nursing or to discontinue the drug, taking into account the importance of the drug to the mother.

Pediatric use

Safety and effectiveness in pediatric patients have not been established.

ADVERSE REACTIONS

In clinical trials, the following local adverse reactions were reported at some point during treatment.

Adverse Experience | Males | Females
Burning | 64% | 78%
Pain | 50% | 72%
Inflammation | 71% | 63%
Erosion | 67% | 67%
Itching | 50% | 65%

Reports of burning and pain were more frequent and of greater severity in women than in men.

Adverse effects reported in less than 5% of the patients included pain with intercourse, insomnia, tingling, bleeding, tenderness, chafing, malodor, dizziness, scarring, vesicle formation, crusting edema, dryness/peeling, foreskin irretraction, hematuria, vomiting and ulceration.

OVERDOSAGE

Topically applied podofilox may be absorbed systemically (see CLINICAL PHARMACOLOGY section). Toxicity reported following systemic administration of podofilox in investigational use for cancer treatment included: nausea, vomiting, fever, diarrhea, bone marrow depression, and oral ulcers. Following 5 to 10 daily intravenous doses of 0.5 to 1 mg/kg/day, significant hematological toxicity occurred but was reversible. Other toxicities occurred at lower doses. Toxicity reported following systemic administration of podophyllum resin included: nausea, vomiting, fever, diarrhea, peripheral neuropathy, altered mental status, lethargy, coma, tachypnea, respiratory failure, leukocytosis, pancytosis, hematuria, renal failure, and seizures. Treatment of topical overdosage should include washing the skin free of any remaining drug and symptomatic and supportive therapy.

DOSAGE AND ADMINISTRATION

In order to ensure that the patient is fully aware of the correct method of therapy and to identify which specific warts should be treated, the technique for initial application of the medication should be demonstrated by the prescriber.

Apply twice daily morning and evening (every 12 hours), for 3 consecutive days, then withhold use for 4 consecutive days. This one week cycle of treatment may be repeated up to four times until there is no visible wart tissue. If there is incomplete response after four treatment weeks, alternative treatment should be considered. Safety and effectiveness of more than four treatment weeks have not been established.

Podofilox 0.5% Solution is applied to the warts with a cotton-tipped applicator supplied with the drug. The drug-dampened applicator should be touched to the wart to be treated, applying the minimum amount of solution necessary to cover the lesion. Treatment should be limited to less than 10 cm^2 of wart tissue and to no more than 0.5 mL of the solution per day. There is no evidence to suggest that more frequent application will increase efficacy, but additional applications would be expected to increase the rate of local adverse reactions and systemic absorption.

Care should be taken to allow the solution to dry before allowing the return of opposing skin surfaces to their normal positions. After each treatment, the used applicator should be carefully disposed of and the patient should wash his or her hands.

HOW SUPPLIED

3.5 mL of Podofilox 0.5% Solution (NDC 54868-6198-0) is supplied as a clear liquid in amber glass bottles with child-resistant screw caps.

Store at controlled room temperature between 15° - 30°C (59° - 86°F).

Avoid excessive heat. Do not freeze.

REFERENCES

1. Berenblum I. The effect of podophyllotoxin on the skin of the mouse, with reference to carcinogenic, cocarcinogenic, and anticarcinogenic action. J Cancer Inst 11: 839-841, 1951.
2. Kaminetzky HA, Swerdlow M. Podophyllin and the mouse cervix: assessment of carcinogenic potential. Am J Obst Gyn 95:486-490, 1965.
3. McGrew EA, Kaminetzky HA. The genesis of experimental cervical epithelial dysplasia. Am J Clin Path 35:538-545, 1961.
4. Roe FJC, Salaman MH. Further studies on incomplete carcinogenesis: triethylene melamine (T.E.M.) 1,2 benxanthracene and beta-propiolactone as initiators of skin tumor formation in the mouse. Brit J Cancer, 9:177-203, 1955.
5. Taper HS. Induction of the deficient acid DNAase activity in mouse interfollicular epidermis by croton oil as a possible tumor promoting mechanism. Zeitschrift fur Krebsforschung and Klinisch Onkologie (Cancer Research and Clinical Oncology, Berlin). 90:197-210, 1977.
6. Kaminetzky HA, McGrew EA, Phillips RL. Experimental cervical epithelial dysplasia. J Obst Gyn 14:1-10, 1959.
7. Kaminetzky HA, McGrew EA: Podophyllin and mouse cervix: Effect of long term application. Arch Path 73:481-485, 1962.
8. Didcock K, Jackson D, Robson JM. The action of some nucleotoxic substances on pregnancy. Brit J Pharmacol 11:437-441, 1956.
9. Thiersch JB. Effect of podophyllin (P) and podophylotoxine (PT) on the rat litter in utero. Soc Exptl Biol Med Proc. 113:124-127, 1963.

Mfd. for: Watson Laboratories, Inc.
Corona, CA 92880 USA
Mfd. by: DPT Laboratories, Ltd.
San Antonio, TX 78215

127937-0103

Relabeling of "Additional Barcode Label" by:
Physicians Total Care, Inc.
Tulsa, OK 74146

PRINCIPAL DISPLAY PANEL

Podofilox 0.5% Solution